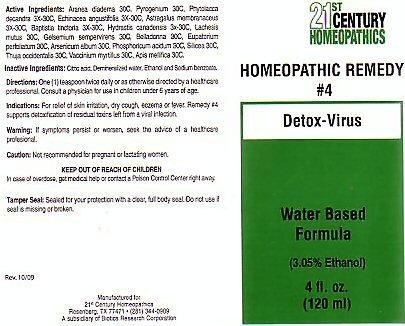 DRUG LABEL: CENTURY 21 DETOX-VIRUS
NDC: 63972-004 | Form: LIQUID
Manufacturer: 21st Century Homeopathics, Inc
Category: homeopathic | Type: HUMAN OTC DRUG LABEL
Date: 20100101

ACTIVE INGREDIENTS: ARANEUS DIADEMATUS 30 [hp_C]/5 mL; RANCID BEEF 30 [hp_C]/5 mL; PHYTOLACCA AMERICANA ROOT 30 [hp_C]/5 mL; ECHINACEA ANGUSTIFOLIA 30 [hp_C]/5 mL; ASTRAGALUS PROPINQUUS ROOT 30 [hp_C]/5 mL; BAPTISIA TINCTORIA ROOT 30 [hp_C]/5 mL; GOLDENSEAL 30 [hp_C]/5 mL; LACHESIS MUTA VENOM 30 [hp_C]/5 mL; GELSEMIUM SEMPERVIRENS ROOT 30 [hp_C]/5 mL; ATROPA BELLADONNA 30 [hp_C]/5 mL; EUPATORIUM PERFOLIATUM FLOWERING TOP 30 [hp_C]/5 mL; ARSENIC TRIOXIDE 30 [hp_C]/5 mL; PHOSPHORIC ACID 30 [hp_C]/5 mL; SILICON DIOXIDE 30 [hp_C]/5 mL; THUJA OCCIDENTALIS LEAFY TWIG 30 [hp_C]/5 mL; BILBERRY 30 [hp_C]/5 mL; APIS MELLIFERA 30 [hp_C]/5 mL
INACTIVE INGREDIENTS: CITRIC ACID MONOHYDRATE; WATER; ALCOHOL; SODIUM BENZOATE

Active Ingredients

Active Ingredients: Aranea diadema 30C, Pyrogenium 30C, Phytolacca decandra 3X-30C, echinacea angustifolia 3X-30C, Astragalus membranaceus 3X-30C, Baptistia tinctoria 3X-30C, Hydrastis canadensis 3X-30C, Lachesis mutus 30C, gelsemium sempervirens 30C, Belladonna 30C, Eupatorium perfoliatum 30C, Arsenicum album 30C, Phosphoricum acidum 30C, Silicea 30C, Thuja occidentalis 30C, Vaccinium myrtillus 30C, Apis mellifica 30C.

Inactive Ingredients

Inactive Ingredients: Citric acid, demineralized water, Ethanol and Sodium benzoate.

Directions For Use

Directions: One (1) teaspoon twice daily or as otherwise directed by a healthcare professional. Consult a physician for use in children under 6 years of age.

Indications

Indications: For relief of skin irritation, dry cough, eczema or fever. Remedy # 4 supports detoxification of residual toxins left from a viral infection.

Keep Out Of Reach Of Children

In case of overdose, get medical help or contact a Poison Control Center right away.

Purpose

Detox-Virus

Warnings

Warning: If symptoms persist or worsen, seek the advice of a healthcare professional.
Caution: Not recommended for pregnant or lactating women.

Product Label

21st CENTURY HOMEOPATHICS
HOMEOPATHIC REMEDY # 4 Detox-Virus
Water based Formula (3.05% Ethanol) 4 fl. oz. (120ml)
Tamper Seal: Sealed for your protection with a clear, full body seal. Do not use if seal is missing or broken.
Rev. 10/09 Manufactured for 21st Century Homeopathics Rosenburg, Tx 77471 (281) 344-0909 A subsidiary of Biotics Research Corporation